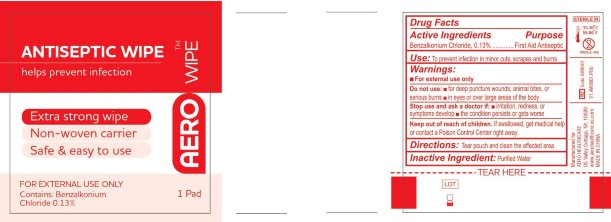 DRUG LABEL: Aerowipe
NDC: 55305-118 | Form: SWAB
Manufacturer: Aero Healthcare
Category: otc | Type: HUMAN OTC DRUG LABEL
Date: 20250801

ACTIVE INGREDIENTS: BENZALKONIUM CHLORIDE 0.1 g/100 g
INACTIVE INGREDIENTS: WATER

Aerowipe Antiseptic Wipe

Active Ingredient

Benzalkonium Chloride, 0.13%

Purpose

First Aid Antiseptic

USE

To prevent infection in minor cuts, scrapes and burns

Warnings:

For external use only

Do not use:

- For deep puncture wounds, animal bites, or serious burns
- In eyes or over large area of the body

Stop use and ask a doctor if:

- Irritation, redness, or symptoms develop
- the condition persists or gets worse

Keep out of reach of children.

If swallowed, get medical help or contact a Poison Control Center right away.

Directions:

Tear pouch and clean the affected area.

Inactive Ingredient

Purified Water